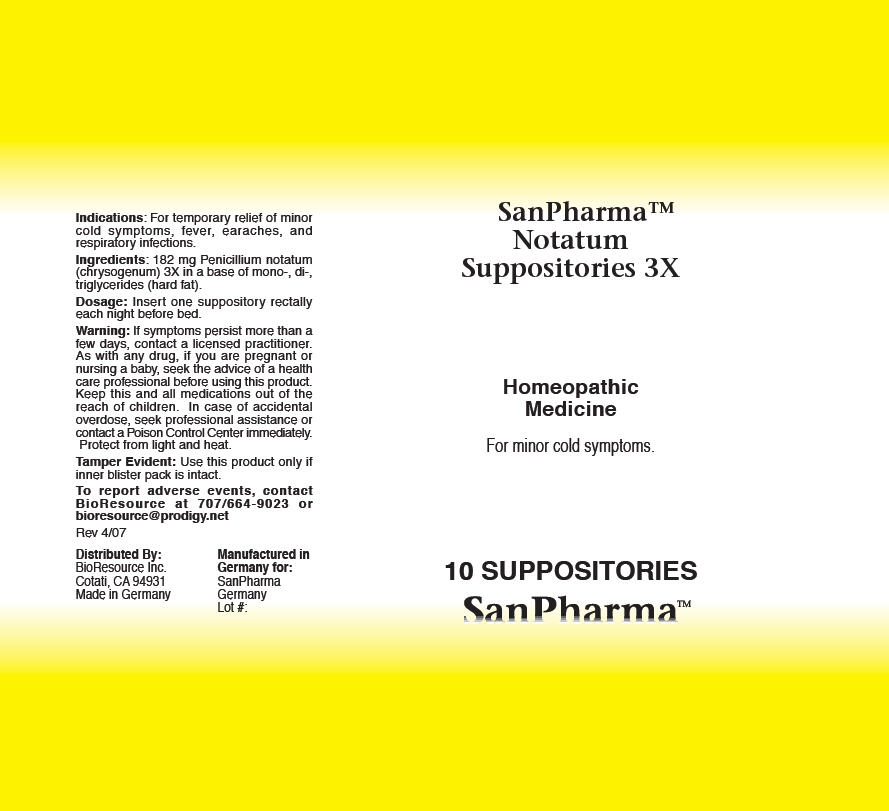 DRUG LABEL: Notatum
NDC: 54256-039 | Form: SUPPOSITORY
Manufacturer: BioResource Inc.
Category: homeopathic | Type: HUMAN OTC DRUG LABEL
Date: 20160722

ACTIVE INGREDIENTS: PENICILLIUM CHRYSOGENUM VAR. CHRYSOGENUM 3 [hp_X]/1 1
INACTIVE INGREDIENTS: FAT, HARD; SODIUM CHLORIDE

Notatum suppositories

Indications

PURPOSE

For temporary relief of minor cold symptoms, fever, earaches, and respiratory infections.

Ingredients

INACTIVE INGREDIENT

182 mg Penicillium notatum (chrysogenum) 3X in a base of mono-, di-, triglycerides (hard fat).

Dosage

Insert one suppository rectally each night before bed.

Warning

If symptoms persist more than a few days, contact a licensed practitioner. As with any drug, if you are pregnant or nursing a baby, seek the advice of a health care professional before using this product.

KEEP OUT OF REACH OF CHILDREN

Keep this and all medications out of the reach of children. In case of accidental overdose, seek professional assistance or contact a Poison Control Center immediately. Protect from light and heat.

Tamper Evident

Use this product only if inner blister pack is intact.

QUESTIONS

To report adverse events, contact BioResource at 707/664-9023 or bioresource@prodigy.net

Distributed By:
BioResource Inc.
Cotati, CA 94931

PRINCIPAL DISPLAY PANEL - 10 Suppository Blister Pack Box

SanPharma™
Notatum
Suppositories 3X

Homeopathic
Medicine

For minor cold symptoms.

10 SUPPOSITORIES
SanPharma™